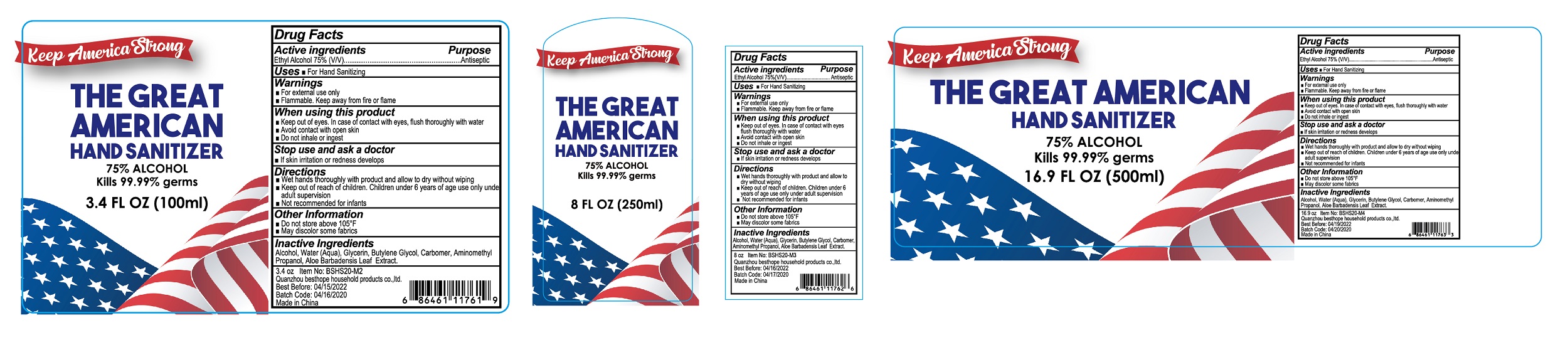 DRUG LABEL: hand sanitizer
NDC: 50049-010 | Form: GEL
Manufacturer: QUANZHOU BESTHOPE HOUSEHOLD PRODUCTS CO.,LTD.
Category: otc | Type: HUMAN OTC DRUG LABEL
Date: 20200705

ACTIVE INGREDIENTS: ALCOHOL 75 mL/100 mL
INACTIVE INGREDIENTS: CARBOMER HOMOPOLYMER, UNSPECIFIED TYPE; AMINOMETHYLPROPANOL; WATER; GLYCERIN; ALOE VERA LEAF; BUTYLENE GLYCOL

50049-010 Hand Sanitizer

Active Ingredient

Ethyl Alcohol 75%

Purpose

Antiseptic

Use

For Hand Sanitizing

WARNINGS

■For extemal use only
■Flammable. Keep away from fire or flame
When using this product
■Keep out of eyes. In case of contact with eyes, flush thoroughly with water
1 Avoid contact with open skin
■Do not inhale or ingest
Stop use and ask a doctor
■If skin irritation or redness develops

■Keep out of reach of children. Children under 6 years of age use only under adult supervision

Directions

Wet hands thoroughly with product and allow to dry without wiping
Not recommended for infants

Inactive ingredients

Alcohol, Water (Aqua), Glycerin, Butylene Glyool, Carbomer, Aminomethyl
Propanol, Aloe Barbadensis Leaf Extract.